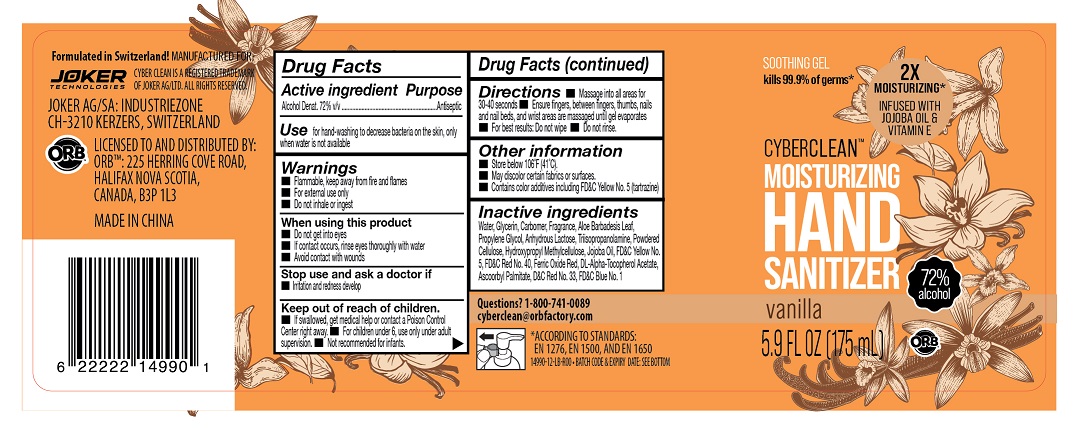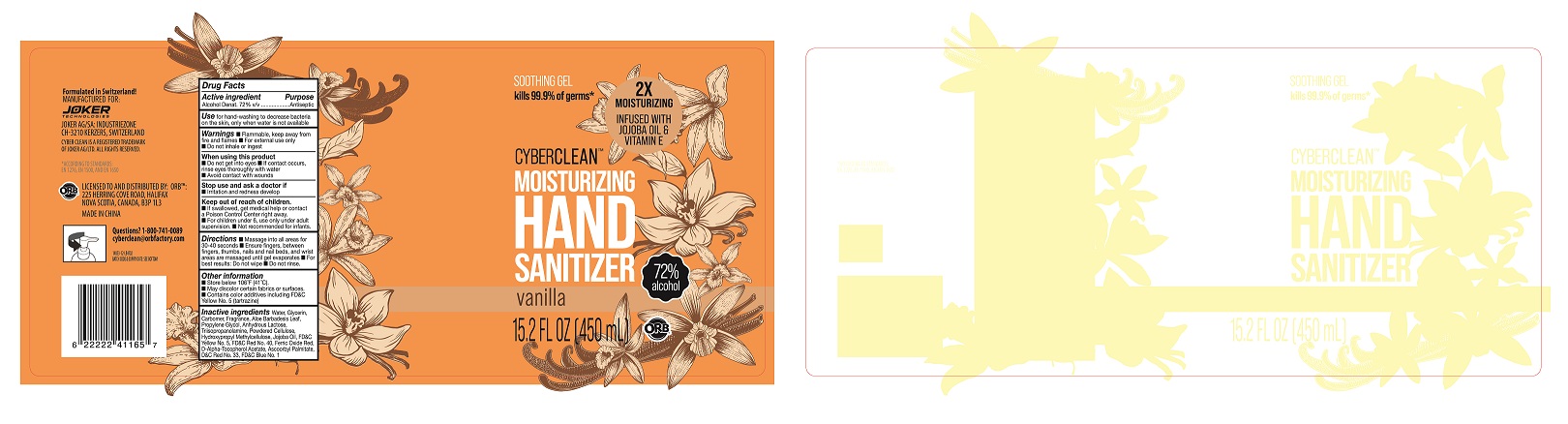 DRUG LABEL: Cyber Clean Moisturizing Hand Sanitizer Vanilla
NDC: 75757-111 | Form: LIQUID
Manufacturer: JOKER AG
Category: otc | Type: HUMAN OTC DRUG LABEL
Date: 20210126

ACTIVE INGREDIENTS: ALCOHOL 72 mL/100 mL
INACTIVE INGREDIENTS: GLYCERIN; ALOE VERA LEAF; WATER; CARBOMER 980; TRIISOPROPANOLAMINE; FERRIC OXIDE RED; PROPYLENE GLYCOL; FD&C YELLOW NO. 5; FD&C BLUE NO. 1; POWDERED CELLULOSE; HYPROMELLOSES; JOJOBA OIL; D&C RED NO. 33; FD&C RED NO. 40; ANHYDROUS LACTOSE; ALPHA-TOCOPHEROL ACETATE; ASCORBYL PALMITATE

Cyber Clean Moisturizing Hand Sanitizer Vanilla

Cyber Clean Moisturizing Hand Sanitizer Vanilla

Active Ingredient(s)

Alcohol 72% v/v. Purpose: Antiseptic

Purpose

Antiseptic, Hand Sanitizer

Use

Hand Sanitizer to help reduce bacteria that potentially can cause disease. For use when soap and water are not available.

Warnings

For external use only. Flammable. Keep away from heat or flame

Do not use

- in children less than 2 months of age
- on open skin wounds

When using this product keep out of eyes, ears, and mouth. In case of contact with eyes, rinse eyes thoroughly with water.
Stop use and ask a doctor if irritation or rash occurs. These may be signs of a serious condition.
Keep out of reach of children. If swallowed, get medical help or contact a Poison Control Center right away.

Stop use and ask a doctor if irritation or rash occurs. These may be signs of a serious condition.

Keep out of reach of children. If swallowed, get medical help or contact a Poison Control Center right away.

Directions

- Place enough product on hands to cover all surfaces. Rub hands together until dry.
- Supervise children under 6 years of age when using this product to avoid swallowing.

Other information

- Store between 15-30C (59-86F)
- Avoid freezing and excessive heat above 40C (104F)

Inactive ingredients

Water
Glycerol
Aloe barbadensis leaf extract
Propylene Glycol
Carbomer 980
Triisopropanolamine
D&C Red 33
FD&C Yellow 5
FD&C Red 40
FD&C Blue 1
Lactose
Cellulose
Hydroxypropyl methylcellulose
Jojoba Esters
Iron oxides
Tocopheryl acetate
Ascorbyl Palmitate